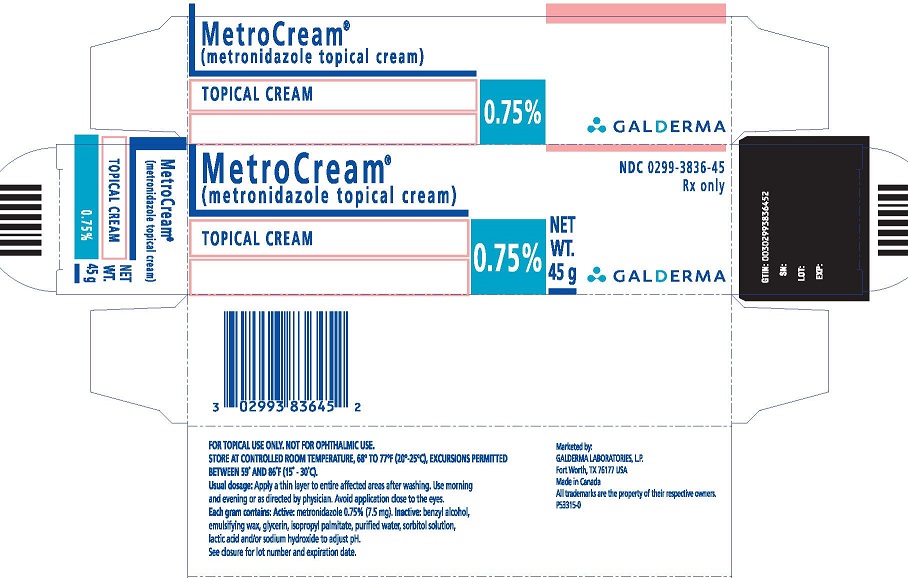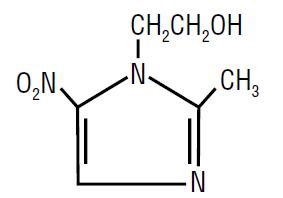 DRUG LABEL: MetroCream 
NDC: 0299-3836 | Form: CREAM
Manufacturer: Galderma Laboratories, L.P.
Category: prescription | Type: HUMAN PRESCRIPTION DRUG LABEL
Date: 20180626

ACTIVE INGREDIENTS: Metronidazole 7.5 mg/1 g
INACTIVE INGREDIENTS: Benzyl Alcohol; Glycerin; Isopropyl Palmitate; Water; Sorbitol; Lactic Acid; Sodium Hydroxide

MetroCream®
(metronidazole topical cream)Topical Cream, 0.75%
Rx Only
FOR TOPICAL USE ONLY
(NOT FOR OPHTHALMIC USE)

DESCRIPTION:

METROCREAM® Topical Cream contains metronidazole, USP, at a concentration of 7.5 mg per gram (0.75%) in an emollient cream consisting of benzyl alcohol, emulsifying wax, glycerin, isopropyl palmitate, purified water, sorbitol solution, lactic acid and/or sodium hydroxide to adjust pH. Metronidazole is a member of the imidazole class of antibacterial agents and is classified therapeutically as an antiprotozoal and anti-bacterial agent. Chemically, metronidazole is 2-methyl-5-nitro-1 H-imidazole-1-ethanol. The molecular formula is C6H9N3O3 and molecular weight is 171.16. Metronidazole is represented by the following structural formula:

CLINICAL PHARMACOLOGY:

The mechanisms by which metronidazole acts in the treatment of rosacea are unknown, but appear to include an anti-inflammatory effect.

INDICATIONS AND USAGE:

METROCREAM® (metronidazole topical cream) Topical Cream is indicated for topical application in the treatment of inflammatory papules and pustules of rosacea.

CONTRAINDICATIONS:

METROCREAM® (metronidazole topical cream) Topical Cream is contraindicated in individuals with a history of hypersensitivity to metronidazole, or other ingredients of the formulation.

PRECAUTIONS:

General: Topical metronidazole has been reported to cause tearing of the eyes. Therefore, contact with the eyes should be avoided. If a reaction suggesting local irritation occurs, patients should be directed to use the medication less frequently or discontinue use. Metronidazole is a nitroimidazole and should be used with care in patients with evidence of, or history of blood dyscrasia.

Information for patients: This medication is to be used as directed by the physician. It is for external use only. Avoid contact with the eyes.

Drug interactions: Oral metronidazole has been reported to potentiate the anticoagulant effect of warfarin and coumarin anticoagulants, resulting in a prolongation of prothrombin time. The effect of topical metronidazole on prothrombin time is not known.

Carcinogenesis, mutagenesis, impairment of fertility: Metronidazole has shown evidence of carcinogenic activity in a number of studies involving chronic, oral administration in mice and rats but not in studies involving hamsters.

Metronidazole has shown evidence of mutagenic activity in several in vitro bacterial assay systems. In addition, a dose-response increase in the frequency of micronuclei was observed in mice after intraperitoneal injections and an increase in chromosome aberrations have been reported in patients with Crohn’s disease who were treated with 200-1200 mg/day of metronidazole for 1 to 24 months. However, no excess chromosomal aberrations in circulating human lymphocytes have been observed in patients treated for 8 months.

Pregnancy: Teratogenic effects: Pregnancy category B: There are no adequate and well-controlled studies with the use of METROCREAM® (metronidazole topical cream) Topical Cream in pregnant women. Metronidazole crosses the placental barrier and enters the fetal circulation rapidly. No fetotoxicity was observed after oral metronidazole in rats or mice. However, because animal reproduction studies are not always predictive of human response and since oral metronidazole has been shown to be a carcinogen in some rodents, this drug should be used during pregnancy only if clearly needed.

Nursing mothers: After oral administration, metronidazole is secreted in breast milk in concentrations similar to those found in the plasma. Even though blood levels are significantly lower with topically applied metronidazole than those achieved after oral administration of metronidazole, a decision should be made whether to discontinue nursing or to discontinue the drug, taking into account the importance of the drug to the mother.

Pediatric use: Safety and effectiveness in pediatric patients have not been established.

ADVERSE REACTIONS:

In controlled clinical trials, the total incidence of adverse reactions associated with the use of METROCREAM® Topical Cream was approximately 10%. Skin discomfort (burning and stinging) was the most frequently reported event followed by erythema, skin irritation, pruritus and worsening of rosacea. All individual events occurred in less than 3% of patients. The following additional adverse experiences have been reported with the topical use of metronidazole: dryness, transient redness, metallic taste, tingling or numbness of extremities and nausea.

DOSAGE AND ADMINISTRATION:

Apply and rub in a thin layer of METROCREAM® (metronidazole topical cream) Topical Cream twice daily, morning and evening, to entire affected areas after washing.

Areas to be treated should be washed with a mild cleanser before application. Patients may use cosmetics after application of METROCREAM® (metronidazole topical cream) Topical Cream.

HOW SUPPLIED:

METROCREAM® (metronidazole topical cream) Topical Cream, 0.75% is supplied in a 45 g aluminum tube - NDC 0299-3836-45.

Storage conditions: STORE AT CONTROLLED ROOM TEMPERATURE, 68° to 77°F (20° to 25°C), EXCURSIONS PERMITTED BETWEEN 59° AND 86°F (15° - 30°C).

Marketed by:
GALDERMA LABORATORIES, L.P.
Fort Worth, Texas 76177 USA
Made in Canada
All trademarks are the property of their respective owners.
P53314-0
Revised: January 2017

PACKAGE LABEL:

MetroCream®
(metronidazole topical cream)

TOPICAL CREAM

0.75%

NET WT. 45 g

NDC 0299-3836-45

Rx only

GALDERMA

FOR TOPICAL USE ONLY. NOT FOR OPHTHALMIC USE.
STORE AT CONTROLLED ROOM TEMPERATURE, 68° TO 77°F (20°-25°C), EXCURSIONS PERMITTED BETWEEN 59° AND 86°F (15° - 30°C).
Usual dosage: Apply a thin layer to entire affected areas after washing. Use morning and evening or as directed by physician. Avoid application close to the eyes.
Each gram contains: Active: metronidazole 0.75% (7.5 mg). Inactive: benzyl alcohol, emulsifying wax, glycerin, isopropyl palmitate, purified water, sorbitol solution, lactic acid and/or sodium hydroxide to adjust pH.
See closure for lot number and expiration date.

Marketed by:
GALDERMA LABORATORIES, L.P.
Fort Worth, TX 76177 USA
Made in Canada
All trademarks are the property of their respective owners.
P53315-0